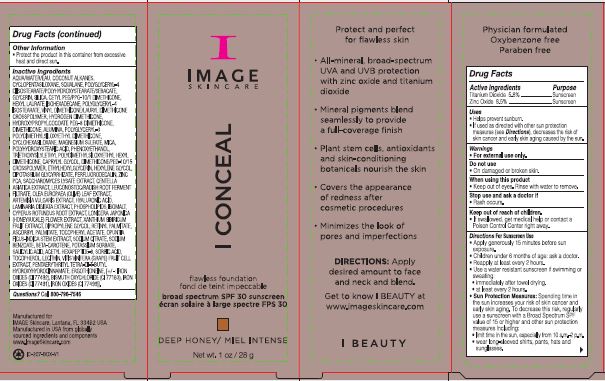 DRUG LABEL: I Conceal Flawless Foundation Broad Spectrum SPF 30 Sunscreen Deep Honey
NDC: 62742-4213 | Form: CREAM
Manufacturer: Allure Labs
Category: otc | Type: HUMAN OTC DRUG LABEL
Date: 20241211

ACTIVE INGREDIENTS: ZINC OXIDE 85 mg/1 g; TITANIUM DIOXIDE 58 mg/1 g
INACTIVE INGREDIENTS: SQUALANE; ISOHEXADECANE; OPUNTIA FICUS-INDICA STEM; SODIUM CITRATE; HEXYL LAURATE; BETA CAROTENE; SALICYLIC ACID; ERGOTHIONEINE; FERRIC OXIDE YELLOW; BISMUTH OXYCHLORIDE; HYDROXYPROPYLCOCOATE PEG-8 DIMETHICONE; ARTEMISIA VULGARIS WHOLE; CYPERUS ROTUNDUS ROOT; XANTHIUM SIBIRICUM FRUIT; VINYL DIMETHICONE/METHICONE SILSESQUIOXANE CROSSPOLYMER; DIMETHICONE; LAMINARIA DIGITATA; OMEGA-3 FATTY ACIDS; .ALPHA.-TOCOPHEROL ACETATE; PERFLUNAFENE; LEUCONOSTOC/RADISH ROOT FERMENT FILTRATE; GLYCERIN; SILICON DIOXIDE; DIMETHICONE/PEG-10/15 CROSSPOLYMER; WINE GRAPE; PENTAERYTHRITOL TETRAKIS(3-(3,5-DI-TERT-BUTYL-4-HYDROXYPHENYL)PROPIONATE); ALUMINUM OXIDE; POLYGLYCERYL-3 POLYDIMETHYLSILOXYETHYL DIMETHICONE (4000 MPA.S); CYCLOMETHICONE 6; DIPROPYLENE GLYCOL; POLYGLYCERYL-4 DIISOSTEARATE/POLYHYDROXYSTEARATE/SEBACATE; CETYL PEG/PPG-10/1 DIMETHICONE (HLB 4); TRIETHOXYSILYLETHYL POLYDIMETHYLSILOXYETHYL HEXYL DIMETHICONE; HYDROGEN DIMETHICONE (13 CST); ETHYLHEXYLGLYCERIN; ACETYL HEXAPEPTIDE-8; SORBIC ACID; TOCOPHEROL; OLEA EUROPAEA LEAF; CAPRYLYL GLYCOL; HEXYLENE GLYCOL; ZINC PIDOLATE; HYALURONIC ACID; ISOMALT; ASCORBYL PALMITATE; LECITHIN, SOYBEAN; FERROSOFERRIC OXIDE; VITAMIN A PALMITATE; CENTELLA ASIATICA TRITERPENOIDS; MAGNESIUM SULFATE, UNSPECIFIED; MICA; GLYCYRRHIZINATE DIPOTASSIUM; LONICERA JAPONICA FLOWER; SACCHAROMYCES LYSATE; POLYGLYCERYL-4 ISOSTEARATE; POLYHYDROXYSTEARIC ACID (2300 MW); PHENOXYETHANOL; FERRIC OXIDE RED; POTASSIUM SORBATE; SODIUM BENZOATE; WATER; COCONUT ALKANES; CYCLOMETHICONE 5

Drug Facts

Active Ingredient

Titanium Dioxide 5.8 %

Zinc Oxide 8.5 %

Purpose

Sunscreen

Uses

Help prevent sunburn

If used as dircted with other sun protection measures (see Directions),

decreases the risk of skin cancer and early skin aging caused by the sun.

Warnings

For external use only

Do not use

On damaged or broken skin

When using this product

Keep out of eyes. Rinse with water to remove

Stop use and aske a doctor if

Rash occurs

Keep out of reach of children

If swallowed, get medical help or contact a

poison control center right away

DOSAGE AND ADMINISTRATION

Directions for sunscreen use

Apply generously 15 minutes before sun exposure

Children under 6 months of age ask doctor

Reapply at least every 2 hours

Use a water resistant sunscreen if swimming or sweating

Immediately after towel drying

at least every 2 hours

OTHER SAFETY INFORMATION

Sun protection measures

spending time in the sun increases your risk of skin cancer and early skin aging to decrease this risk,

regularly use a suncreen with a broad spectrum SPF valu of 15 or higer and other sun protection

measures including

limit time in the sun,especially from 10 am -2 pm

wear long sleeved shirts, pants,hats and sunglassess

Other information

Protect the product in this container from excessive heat and direct sun.

INACTIVE INGREDIENT

AQUA/WATER/EAU,COCONUT ALKANES,

CYCLOPENTASILOXANE,SQUALANE,POLYGLYCERYL-4 DIISOSTEARATE/POLYHYDROXYSTEARATE/SEBACATE

GLYCERIN,SILICA,CETYL PEG/PPG-10/1 DIMETHICONE,

HEXYL LAURATE,ISOHEXADECANE,POLYGLYCERYL-4 ISOSTEARATE,

VINYL DIMETHICONE/LAURYL DIMETHICONE CROSSPOLYMER,

HYDROGEN DIMETHICONE,HYDROXYPROPYLCOCOATE PEG-8 DIMETHICONE,

DIMETHICONE,ALUMINA,POLYGLYCERYL-3 POLYDIMETHYLSILOXYETHYL DIMETHICONE,

CYCLOHEXASILOXANE,MAGNESIUM SULFATE,MICA,

POLYHYDROXYSTEARIC ACID,PHENOXYETHANOL,

TRIETHOXYSIMETHYL POLYDIMETHYLSILOXYETHYL HEXYL DIMETHICONE,

CAPRYLYL GLYCOL,DIMETHICONE/PEG-10/15 CROSSPOLYMER,

ETHYLHEXYLGLYCERIN,HEXYLENE GLYCOL,DIPOTASSIUM GLYCYRRHIZATE,

PERFLUORODECALIN,ZINC PCA,SACCHAROMYCES LYSATE EXTRACT,

CENTELLA ASIATICA EXTRACT,LEUCONOSTOC/RADISH ROOT FERMENT FILTRATE,

OLEA EUROPAEA (OLIVE) LEAF EXTRACT,ARTEMISIA VULGARIS EXTRACT,

HYALURONIC ACID,LAMINARIA DIGITATA EXTRACT,PHOSPHOLIPIDS,ISOMALT,

CYPERUS ROTUNDUS ROOT EXTRACT,LONICERA JAPONICA (HONEYSUCKLE) FLOWER EXTRACT,

XANTHIUM SIBIRICUM FRUIT EXTRACT,DIPROPYLENE GLYCOL,RETINYL PALMITATE,

ASCORBYL PALMITATE,TOCOPHERYL ACETATE,OPUNTIA FICUS-INDICA STEM EXTRACT,

SODIUM CITRATE,SODIUM BENZOATE,BETA-CAROTENE,POTASSIUM SORBATE,

SALICYLIC ACID,ACETYL HEXAPEPTIDE-8,SORBIC ACID,TOCOPHEROL,LECITHIN,

VITIS VINIFERA (GRAPE) FRUIT CELL EXTRACT,PENTAERYTHRITYL TETRA-DI-T-BUTYL

HYDROXYHYDROCINNAMATE,ERGOTHIONEINE,[+/ -: IRON OXIDES (CI 77492),

BISMUTH OXYCHLORIDE (CI 77163),IRON OXIDES (CI 77491),IRON OXIDES (CI 77499)].